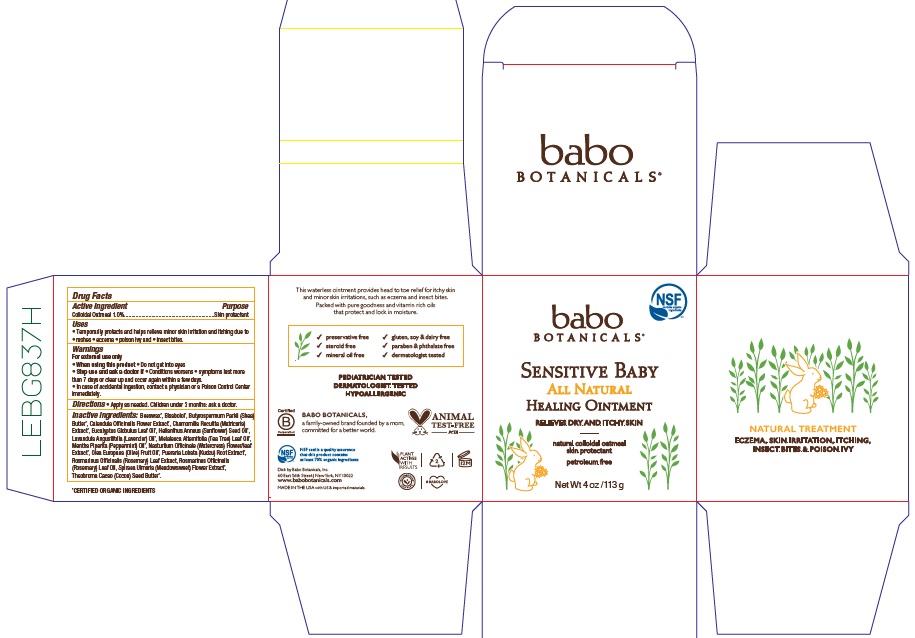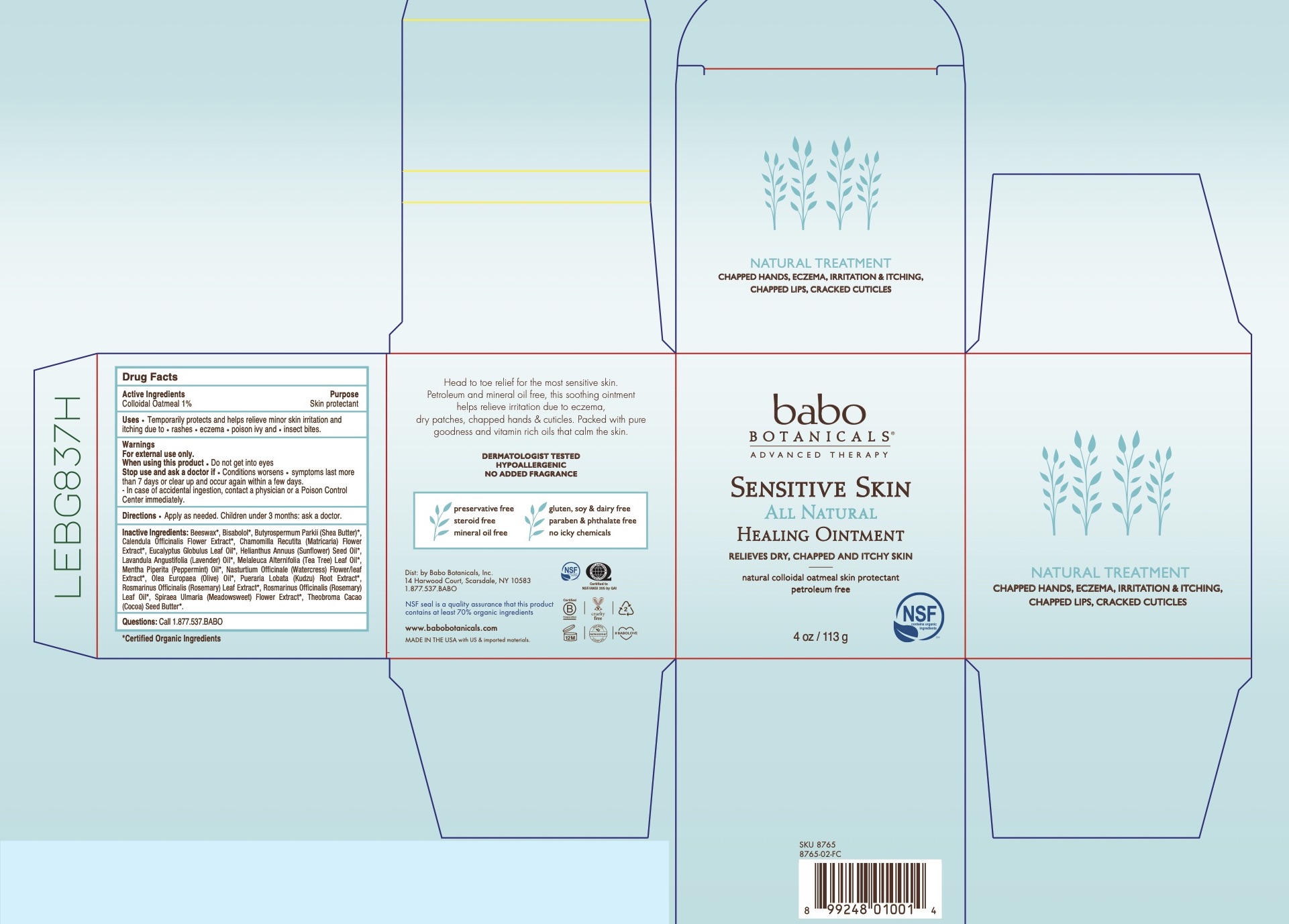 DRUG LABEL: Babo Sensitive Baby All Natural Healing
NDC: 79265-8765 | Form: OINTMENT
Manufacturer: Babo Botanicals, Inc.
Category: otc | Type: HUMAN OTC DRUG LABEL
Date: 20241212

ACTIVE INGREDIENTS: OATMEAL 1 g/100 g
INACTIVE INGREDIENTS: LEVOMENOL 0.1 mL/100 g; OLIVE OIL 10 mL/100 g; PUERARIA MONTANA VAR. LOBATA ROOT 0.0015 mL/100 g; FILIPENDULA ULMARIA FLOWER 0.0015 mL/100 g; COCOA BUTTER 0.01 mL/100 g; SHEA BUTTER 0.01 mL/100 g; EUCALYPTUS OIL 0.25 mL/100 g; CHAMOMILE 0.0015 mL/100 g; WHITE WAX 25 mL/100 g; CALENDULA OFFICINALIS FLOWER 0.0015 mL/100 g; SUNFLOWER OIL 63.2725 mL/100 g; LAVENDER OIL 0.06 mL/100 g; TEA TREE OIL 0.05 mL/100 g; PEPPERMINT OIL 0.1 mL/100 g; NASTURTIUM OFFICINALE FLOWERING TOP 0.0015 mL/100 g; ROSEMARY 0.04 mL/100 g; ROSEMARY OIL 0.1 mL/100 g

8565 & 8765 Babo Sensitive Baby All Natural Healing Ointment

Active Ingredients

Colloidal Oatmeal 1% Skin protectant

Purpose

Skin Protectant

Uses

Temporarily protects and helps relieve minor skin irritation and itching due to • rashes • eczema • poison ivy and • insect bites.

Warnings

For external use only.When using this product • Do not get into eyes Stop use and ask a doctor if• Conditions worsens• symptoms last more than 7 days or clear up and occur again within a few days. - In case of accidental ingestion, contact a physician or a Poison Control Center immediately.

When using this product Do not get into eyes

Stop use and ask a doctor if• Conditions worsens• symptoms last more than 7 days or clear up and occur again within a few days. - In case of accidental ingestion, contact a physician or a Poison Control Center immediately.

Directions

Apply as needed. Children under 3 months: ask a doctor.

Keep out of reach of children

Inactive Ingredients

Beeswax*, Bisabolol*, Butyrospermum Parkii (Shea) Butter*, Calendula Officinalis Flower Extract*, Chamomilla Recutita (Matricaria) Extract*, Eucalyptus Globulus Leaf Oil*, Helianthus Annuus (Sunflower) Seed Oil*, Lavandula Angustifolia (Lavender) Oil*, Melaleuca Alternifolia (Tea Tree) Leaf Oil*, Mentha Piperita (Peppermint) Oil*, Nasturtium Officinale (Watercress) Flower/leaf Extract*, Olea Europaea (Olive) Fruit Oil*, Pueraria Lobata (Kudzu) Root Extract*, Rosmarinus Officinalis (Rosemary) Leaf Extract*, Rosmarinus Officinalis (Rosemary) Leaf Oil*, Spiraea Ulmaria (Meadowsweet) Flower Extract*, Theobroma Cacao (Cocoa) Seed Butter*.

*Certified Organic Ingredient

Distributed by

Dist: by Babo Botanicals, Inc.

60 East 56th Street

New York, NY 10022

Information Panel

This waterless ointment provides head to toe relief for itchy skin and minor skin irritations, such as eczema and insect bites.

Packed with pure goodness and vitamin rich oils that protect and lock in moisture.

gluten, soy & dairy free

paraben & phthalate free

dermatologist tested

preservative free

steroid free

mineral oil free

PEDIATRICIAN TESTED

DERMATOLOGIST TESTED

HYPOALLERGENIC

79265-8565 Principal Display Panel

79265-8565-0 113 g Outer Packaging Box

79265-8765 Principal Display Panel

79265-8765-0 Principal Display Panel